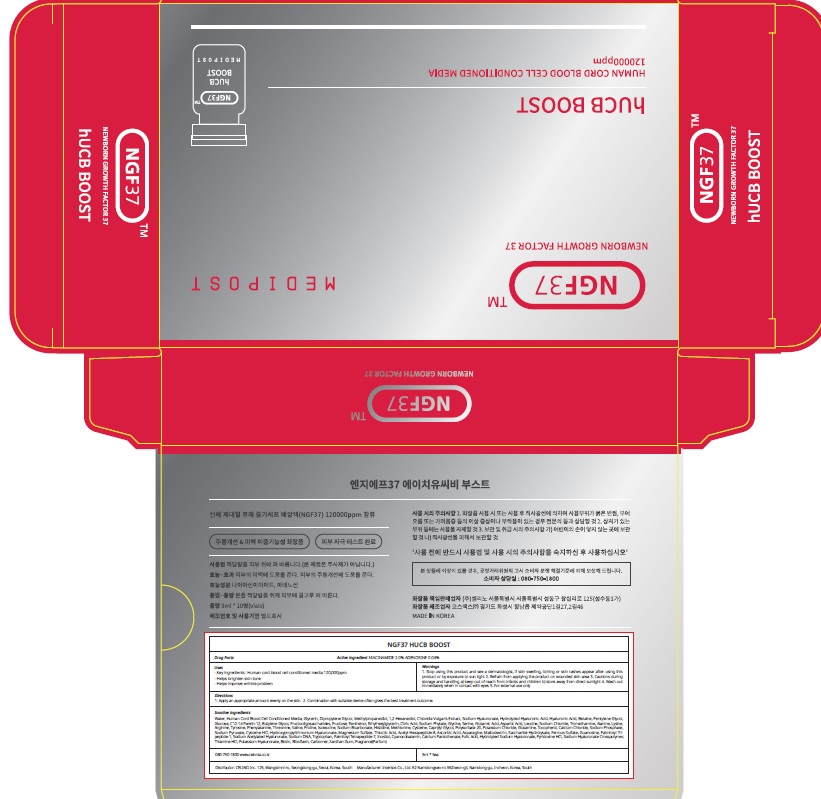 DRUG LABEL: NGF37 hUCB BOOST
NDC: 73655-120 | Form: LIQUID
Manufacturer: Celino Inc.
Category: otc | Type: HUMAN OTC DRUG LABEL
Date: 20211029

ACTIVE INGREDIENTS: NIACINAMIDE 2 g/100 mL; ADENOSINE 0.04 g/100 mL
INACTIVE INGREDIENTS: Water; Glycerin; Dipropylene Glycol

ACTIVE INGREDIENTS

NIACINAMIDE 2.0%
ADENOSINE 0.04%

INACTIVE INGREDIENTS

Water, Human Cord Blood Cell Conditioned Media, Glycerin, Dipropylene Glycol, Methylpropanediol, 1,2-Hexanediol, Chlorella Vulgaris Extract, Sodium Hyaluronate, Hydrolyzed Hyaluronic Acid, Hyaluronic Acid, Betaine, Pentylene Glycol, Glucose, C12-14 Pareth-12, Butylene Glycol, Fructooligosaccharides, Fructose, Panthenol, Ethylhexylglycerin, Citric Acid, Sodium Phytate, Glycine, Serine, Glutamic Acid, Aspartic Acid, Leucine, Sodium Chloride, Tromethamine, Alanine, Lysine, Arginine, Tyrosine, Phenylalanine, Threonine, Valine, Proline, Isoleucine, Sodium Bicarbonate, Histidine, Methionine, Cysteine, Caprylyl Glycol, Polysorbate 20, Potassium Chloride, Glutamine, Tocopherol, Calcium Chloride, Sodium Phosphate, Sodium Pyruvate, Cysteine HCl, Hydroxypropyltrimonium Hyaluronate, Magnesium Sulfate, Thioctic Acid, Acetyl Hexapeptide-8, Ascorbic Acid, Asparagine, Maltodextrin, Saccharide Hydrolysate, Ferrous Sulfate, Guanosine, Palmitoyl Tripeptide-1, Sodium Acetylated Hyaluronate, Sodium DNA, Tryptophan, Palmitoyl Tetrapeptide-7, Inositol, Cyanocobalamin, Calcium Pantothenate, Folic Acid, Hydrolyzed Sodium Hyaluronate, Pyridoxine HCl, Sodium Hyaluronate Crosspolymer, Thiamine HCl, Potassium Hyaluronate, Biotin, Riboflavin, Carbomer, Xanthan Gum, Fragrance(Parfum)

PURPOSE

Skin Brightening
Anti wrinkle

WARNINGS

1. Stop using this product and see a dermatologist, if skin swelling, itching or skin rashes appear after using this product or by exposure to sun light 2. Refrain from applying the product on wounded skin area 3. Cautions during storage and handling a) keep out of reach from infants and children b) store away from direct sunlight 4. Wash out immediately when in contact with eyes 5. For external use only

KEEP OUT OF REACH OF CHILDREN

keep out of reach from infants and children

Uses

■ Key ingredients : Human cord blood cell conditioned media 120,000ppm
■ Helps brighten skin tone
■ Helps improve wrinkle problem

Directions

1. Apply an appropriate amount evenly on the skin.
2. Combination with suitable device often gives the best treatment outcome.

QUESTIONS

080-750-1800 www.celonia.co.kr